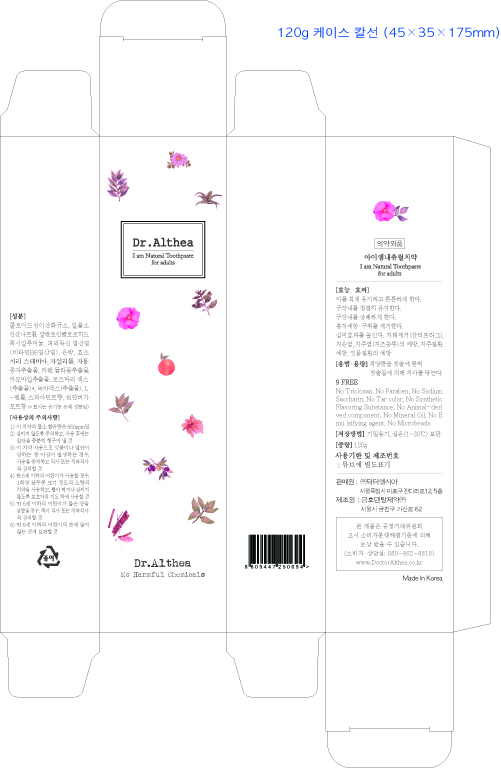 DRUG LABEL: Dr.Althea I am Natural ToothpasteForAdults
NDC: 70905-0017 | Form: PASTE, DENTIFRICE
Manufacturer: Dr. Althea
Category: otc | Type: HUMAN OTC DRUG LABEL
Date: 20180322

ACTIVE INGREDIENTS: SODIUM MONOFLUOROPHOSPHATE 0.5 g/100 g
INACTIVE INGREDIENTS: SILICON DIOXIDE; PYRIDOXINE HYDROCHLORIDE

ACTIVE INGREDIENT

SODIUM MONOFLUOROPHOSPHATE, SILICA, PYRIDOXINE HCI, ALCLOXA

PURPOSE

Aids in the prevention of dental cavities.

Keep out of reach of children

INDICATIONS AND USAGE

How to use:

1) Squeeze toothpaste on to toothbrush.
2) Brush thoroughly at least twice a day.
3) Brush for 3+ minutes.
4) Rinse out thoroughly with water.

Directions

■ Adults and children 2 years of age and older: Brush teeth thoroughly, preferably after each meal or at least twice a day, or as directed by a dentist or doctor.

■ Instruct children under 6 years of age in good brushing and rinsing habits (to minimize swallowing).

■ Supervise children as necessary until capable of using without supervision.

■ Children under 2 years of age: Consult a dentist or doctor.

WARNINGS

Cautions:
1) If following symptoms occur after product use, stop using immediately: red spots, swelling, itchiness, and other skin irritations. 2) Avoid contact with eyes and open wounds. 3) Keep out of reach of children. 4) Do not store at high/low temperature. 5) Avoid direct sunlight.

■ If more than used for brushing is accidentally swallowed, get medical help or contact a Poison Control Center right away.

INACTIVE INGREDIENT

SILVER, HYDRATED SILICA, CELLULOSE GUM, SORBITIOL, GLYCERIN, PEG-32, XYLITOL, MENTHOL, WATER, ETC.

DOSAGE AND ADMINISTRATION

For dental use only